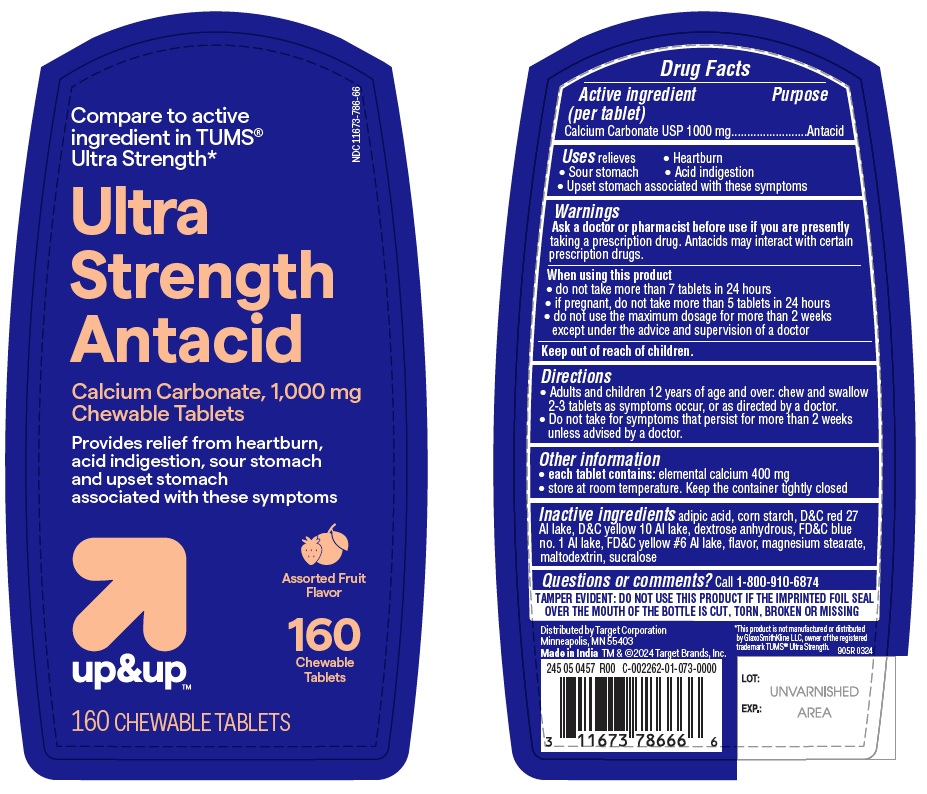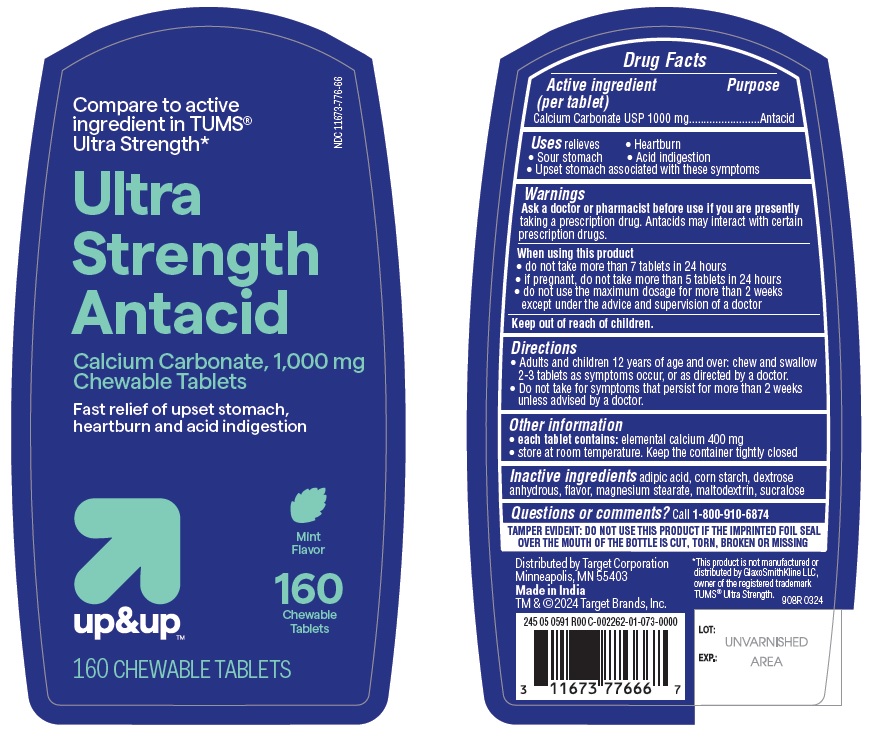 DRUG LABEL: Ultra Strength Antacid
NDC: 11673-786 | Form: TABLET, CHEWABLE
Manufacturer: TARGET CORPORATION
Category: otc | Type: HUMAN OTC DRUG LABEL
Date: 20251104

ACTIVE INGREDIENTS: CALCIUM CARBONATE 1000 mg/1 1
INACTIVE INGREDIENTS: D&C RED NO. 27 ALUMINUM LAKE; ADIPIC ACID; MAGNESIUM STEARATE; ANHYDROUS DEXTROSE; FD&C BLUE NO. 1 ALUMINUM LAKE; SUCRALOSE; STARCH, CORN; D&C YELLOW NO. 10 ALUMINUM LAKE; FD&C YELLOW NO. 6 ALUMINUM LAKE; MALTODEXTRIN

Target_Calcium Carbonate 1000mg Ultra Strength-Assorted fruit / Peppermint

Active ingredient (per tablet)

Calcium Carbonate USP 1000 mg

Purpose

Antacid

INDICATIONS AND USAGE

Uses relieves

- Heartburn
- Sour stomach
- Acid indigestion
- Upset stomach associated with these symptoms

Ask a doctor or pharmacist before use if you are presently taking a prescription drug. Antacids may interact with certain prescription drugs.

When using this product

- do not take more than 7 tablets in 24 hours
- if pregnant, do not take more than 5 tablets in 24 hours
- do not use the maximum dosage for more than 2 weeks except under the advice and supervision of a doctor.

Keep out of reach of children.

Directions

- Adults and children 12 years of age and over: chew and swallow 2-3 tablets as symptoms occur, or as directed by a doctor.
- Do not take for symptoms that persist for more than 2 weeks unless advised by a doctor.

Other information

- each tablet contains: elemental calcium 400 mg
- store at room temperature. Keep the container tightly closed

INACTIVE INGREDIENT

Calcium Carbonate 1000 mg Chewable Tablets - Assorted Fruit (Ultra Strength)

Inactive ingredients adipic acid, corn starch, D&C red 27 Al lake, D&C yellow 10 Al lake, dextrose anhydrous, FD&C blue no. 1 Al lake, FD&C yellow #6 Al lake, flavor, magnesium stearate, maltodextrin, sucralose

Calcium Carbonate 1000 mg Chewable Tablets - Peppermint (Ultra Strength)

Inactive ingredients

adipic acid, corn starch, dextrose anhydrous, flavor, magnesium stearate, maltodextrin, sucralose

Questions or comments? Call 1-800-910-6874